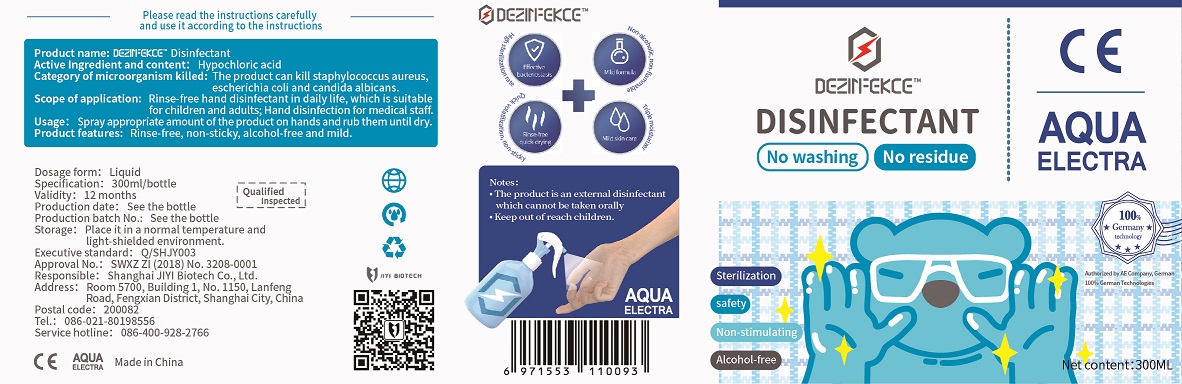 DRUG LABEL: DEZINFEKCE Disinfectant
NDC: 75316-103 | Form: LIQUID
Manufacturer: Shanghai Jiyi Biological Technology Co., Ltd.
Category: otc | Type: HUMAN OTC DRUG LABEL
Date: 20200423

ACTIVE INGREDIENTS: HYPOCHLOROUS ACID 210 mg/300 mL
INACTIVE INGREDIENTS: WATER; SODIUM CHLORIDE

JiYi, DEZINFEKCE Disinfectant, Liquid, 300mL

Active Ingredient(s)

Hypochlorous acid 700 mg/L. Purpose: Kill microorganism.

Purpose

Rinse-free hand disinfectant in daily life, which is suitable for children and adults; Hand disinfection for medical staff.

The product can kill staphylococcus aureus, escherichia coli and candida albicans.

Use

Spray appropriate amount of the product on hands and rub them until dry.

Warnings

External Use Only

•Do not replace containers

•Do not mix it with other disinfection products

•Keep it sealed, and use it as soon as possible after unpacking

•Spraying on the fabrics is not recommended

•Not suitable for articles made of copper or carbon steel

•Keep out of reach children

Do not use

- on children less than 2 months of age
- on open skin wounds
- mixing this product with other disinfectants

When using this product keep out of eyes, ears, and mouth.

In case of contact with eyes, rinse eyes thoroughly with water.

This product is for external use. It should not be taken orally.

This product has a certain corrosive effect on metal objects other than stainless steel, and should be used with caution.

When sterilizing articles containing more organic objects, they should be completely removed and then disinfected.

Use with caution for those with sensitive skin.

Do not mix this product with other disinfectants.

Stop use and ask a doctor if irritation or rash occurs. These may be signs of a serious condition.

Directions

Spray appropriate amount of the product on hands and rub them until dry

Other information

Storage: place it in a normal temperature and light-shielded environment.

Inactive ingredients

Sodium chloride, Water